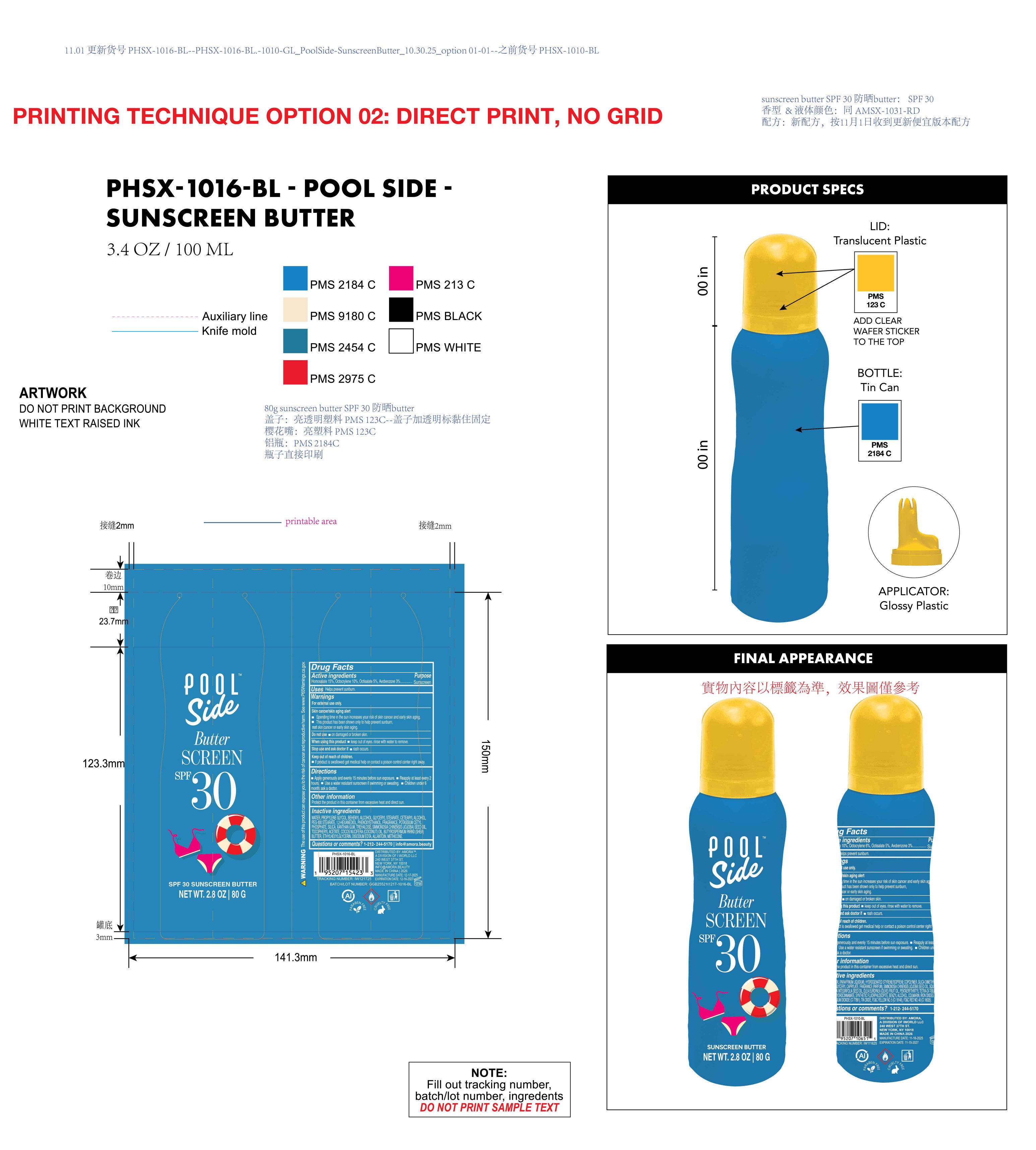 DRUG LABEL: Poolside Butter SCREEN SPF 30 sunscreen Butter
NDC: 85161-165 | Form: OIL
Manufacturer: Longway Technology(Guangzhou)Co.,Ltd.
Category: otc | Type: HUMAN OTC DRUG LABEL
Date: 20251204

ACTIVE INGREDIENTS: OCTISALATE 0.05 g/1 g; AVOBENZONE 0.03 g/1 g; HOMOSALATE 0.15 g/1 g; OCTOCRYLENE 0.1 g/1 g
INACTIVE INGREDIENTS: FRAGRANCE 13576; ALPHA-TOCOPHEROL ACETATE; SILICA; EDETATE DISODIUM; PROPYLENE GLYCOL; SIMMONDSIA CHINENSIS (JOJOBA) SEED OIL; ALLANTOIN; METHICONE (20 CST); XANTHAN GUM; PEG-100 STEARATE; PHENOXYETHANOL; WATER; ETHYLHEXYLGLYCERIN; TREHALOSE; POTASSIUM CETYL PHOSPHATE; COCOS NUCIFERA (COCONUT) OIL; BUTYROSPERMUM PARKII (SHEA) BUTTER; BEHENYL ALCOHOL; GLYCERYL STEARATE; 1,2-HEXANEDIOL; CETEARYL ALCOHOL

ACTIVE INGREDIENT

Homosalate 15%, Octocrylene 10%, Octisalate 5% , Avobenzone 3%

PURPOSE

Sunscreen

INDICATIONS AND USAGE

Helps prevent sunburn.

KEEP OUT OF REACH OF CHILDREN

If product is swallowed get medical help or contact a poison control center right away.

QUESTIONS

1-212-244-5170|info@amora.beauty

DOSAGE AND ADMINISTRATION

Apply generously and evenly 15 minutes before sun exposure.

Reapply at least every 2 hours.

Use a water resistant sunscreen if swimming or sweating.

Children under 6 month: ask a doctor.

WARNINGS

For external use only.

Skin cancer/skin aging alert
Spending time in the sun increases your risk of skin cancer and early skin aging.

This product has been shown only to help prevent sunburn,not skin cancer or early skin aging.
Do not use m on damaged or broken skin.
When using this product keep out of eves. rinse with water to remove
Stop use and ask doctor if rash occurs.

Keep out of reach of children.
lf product is swallowed get medical help or contact a poison control center right away.

OTHER SAFETY INFORMATION

Protect the product in this container from excessive heat and direct sun.

INACTIVE INGREDIENT

WATER，PROPYLENE GLYCOL，BEHENYL ALCOHOL，GLYCERYL STEARATE，CETEARYL ALCOHOL，PEG-100 STEARATE，1,2-HEXANEDIOL，PHENOXYETHANOL，FRAGRANCE，POTASSIUM CETYL PHOSPHATE，SILICA，XANTHAN GUM，TREHALOSE，SIMMONDSIA CHINENSIS (JOJOBA) SEED OIL，TOCOPHERYL ACETATE，COCOS NUCIFERA (COCONUT) OIL，BUTYROSPERMUM PARKII (SHEA) BUTTER，ETHYLHEXYLGLYCERIN，DISODIUM EDTA，ALLANTOIN，METHICONE